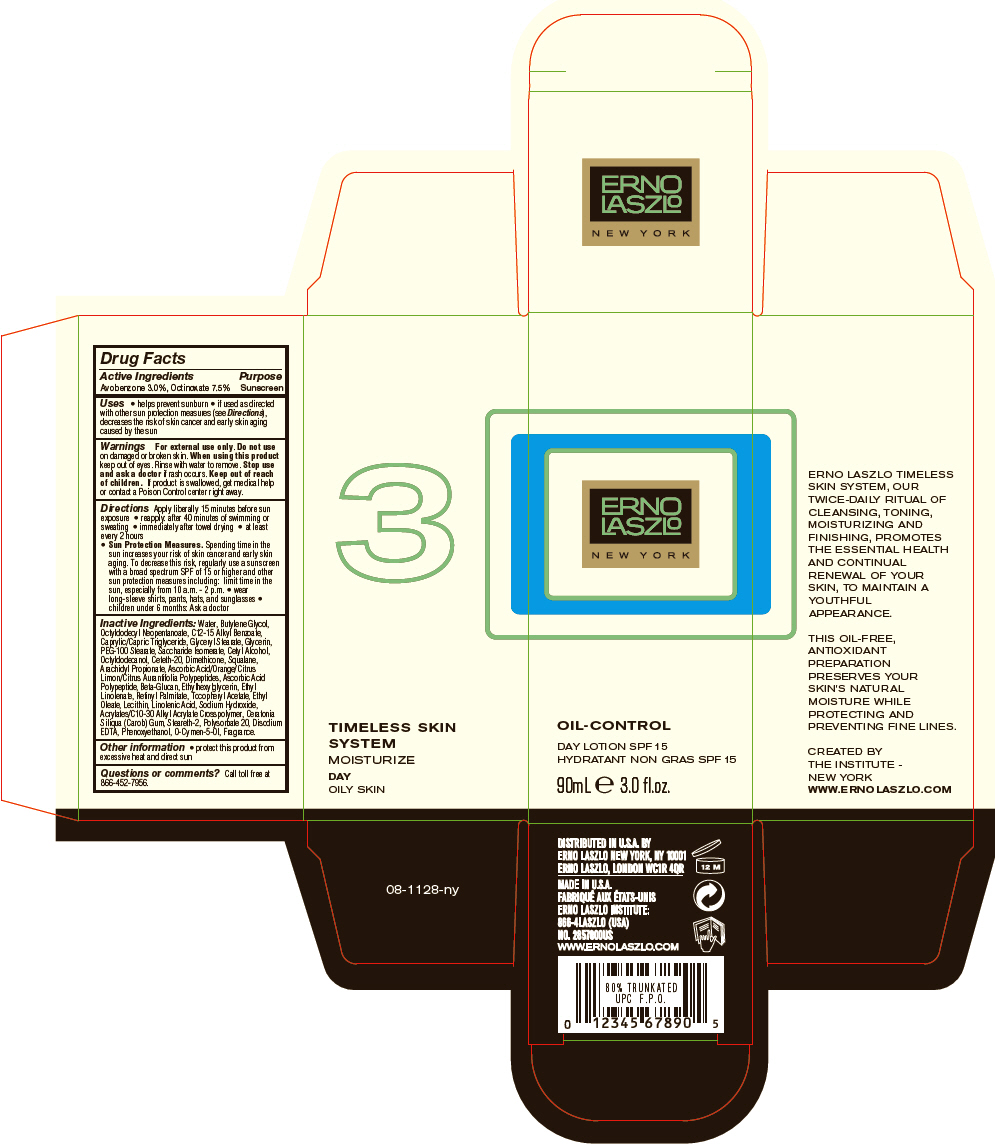 DRUG LABEL: Oil-Control Day  SPF 15
NDC: 57913-2857 | Form: LOTION
Manufacturer: Erno Laszlo, Inc.
Category: otc | Type: HUMAN OTC DRUG LABEL
Date: 20130409

ACTIVE INGREDIENTS: Avobenzone 30 mg/1 mL; Octinoxate 75 mg/1 mL
INACTIVE INGREDIENTS: WATER; BUTYLENE GLYCOL; OCTYLDODECYL NEOPENTANOATE; ALKYL (C12-15) BENZOATE; MEDIUM-CHAIN TRIGLYCERIDES; GLYCERYL MONOSTEARATE; GLYCERIN; PEG-100 STEARATE; SACCHARIDE ISOMERATE; CETYL ALCOHOL; OCTYLDODECANOL; CETETH-20; DIMETHICONE; SQUALANE; ARACHIDYL PROPIONATE; ETHYLHEXYLGLYCERIN; ETHYL LINOLENATE; VITAMIN A PALMITATE; .ALPHA.-TOCOPHEROL ACETATE; ETHYL OLEATE; LINOLENIC ACID; SODIUM HYDROXIDE; LOCUST BEAN GUM; STEARETH-2; POLYSORBATE 20; EDETATE DISODIUM; PHENOXYETHANOL; O-CYMEN-5-OL

Oil-Control Day SPF 15

Drug Facts

Active Ingredients

Avobenzone 3.0%, Octinoxate 7.5%

Purpose

Sunscreen

Uses

- helps prevent sunburn
- if used as directed with other sun protection measures (see Directions), decreases the risk of skin cancer and early skin aging caused by the sun

Warnings

For external use only.

Do not use on damaged or broken skin.

When using this product keep out of eyes. Rinse with water to remove.

Stop use and ask a doctor if rash occurs.

Keep out of reach of children. If product is swallowed, get medical help or contact a Poison Control center right away.

Directions

Apply liberally 15 minutes before sun exposure

- reapply: after 40 minutes of swimming or sweating
- immediately after towel drying
- at least every 2 hours
- Sun Protection Measures. Spending time in the sun increases your risk of skin cancer and early skin aging. To decrease this risk, regularly use a sunscreen with a broad spectrum SPF of 15 or higher and other sun protection measures including: limit time in the sun, especially from 10 a.m. - 2 p.m.
  - wear long-sleeve shirts, pants, hats, and sunglasses
  - children under 6 months: Ask a doctor

Inactive Ingredients

Water, Butylene Glycol, Octyldodecyl Neopentanoate, C12-15 Alkyl Benzoate, Caprylic/Capric Triglyceride, Glyceryl Stearate, Glycerin, PEG-100 Stearate, Saccharide Isomerate, Cetyl Alcohol, Octyldodecanol, Ceteth-20, Dimethicone, Squalane, Arachidyl Propionate, Ascorbic Acid/Orange/Citrus Limon/Citrus Aurantifolia Polypeptides, Ascorbic Acid Polypeptide, Beta-Glucan, Ethylhexylglycerin, Ethyl Linolenate, Retinyl Palmitate, Tocopheryl Acetate, Ethyl Oleate, Lecithin, Linolenic Acid, Sodium Hydroxide, Acrylates/C10-30 Alkyl Acrylate Crosspolymer, Ceratonia Siliqua (Carob) Gum, Steareth-2, Polysorbate 20, Disodium EDTA, Phenoxyethanol, O-Cymen-5-Ol, Fragrance.

Other information

- protect this product from excessive heat and direct sun

Questions or comments?

Call toll free at 866-452-7956.

DISTRIBUTED IN U.S.A. BY ERNO LASZLO NEW YORK, NY 10001

PRINCIPAL DISPLAY PANEL - 90 mL Bottle Carton

ERNO
LASZLO

NEW YORK

OIL-CONTROL

DAY LOTION SPF 15

90mL e 3.0 fl.oz.